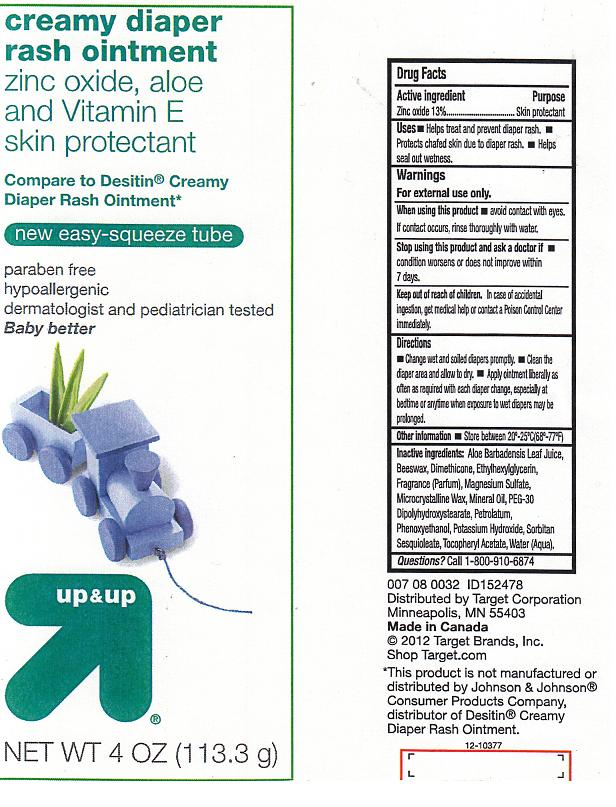 DRUG LABEL: UP and UP
NDC: 11673-332 | Form: OINTMENT
Manufacturer: TARGET CORPORATION
Category: otc | Type: HUMAN OTC DRUG LABEL
Date: 20120424

ACTIVE INGREDIENTS: ZINC OXIDE 13.0 g/100 g
INACTIVE INGREDIENTS: ALOE VERA LEAF; APIS MELLIFERA; DIMETHICONE; ETHYLHEXYLGLYCERIN; MAGNESIUM SULFATE; MICROCRYSTALLINE WAX; MINERAL OIL; PEG-30 DIPOLYHYDROXYSTEARATE; PETROLATUM; PHENOXYETHANOL; POTASSIUM HYDROXIDE; SORBITAN SESQUIOLEATE; ALPHA-TOCOPHEROL ACETATE; WATER

DRUG FACTS

ACTIVE INGREDIENT

ZINC OXIDE 13%

PURPOSE

SKIN PROTECTANT

USES

HELPS TREAT AND PREVENT DIAPER RASH. PROTECTS CHAFED SKIN DUE TO DIAPER RASH. HELPS SEAL OUT WETNESS.

WARNINGS

FOR EXTERNAL USE ONLY.

WHEN USING THIS PRODUCT

AVOID CONTACT WITH EYES. IF CONTACT OCCURS, RINSE THOROUGHLY WITH WATER.

STOP USING THIS PRODUCT AND ASK A DOCTOR IF

CONDITION WORSENS OR DOES NOT IMPROVE WITHIN 7 DAYS.

KEEP OUT OF REACH OF CHILDREN

IN CASE OF ACCIDENTAL INGESTION, GET MEDICAL HELP OR CONTACT A POISON CONTROL CENTER IMMEDIATELY.

DIRECTIONS

CHANGE WET AND SOILED DIAPERS PROMPTLY. CLEAN THE DIAPER AREA AND ALLOW TO DRY. APPLY OINTMENT LIBERALLY AS OFTEN AS REQUIRED WITH EACH DIAPER CHANGE, ESPECIALLY AT BEDTIME OR ANYTIME WHEN EXPOSURE TO WET DIAPERS MAY BE PROLONGED.

OTHER INFORMATION

STORE BETWEEN 20-25C (68-77F).

INACTIVE INGREDIENTS:

ALOE BARBADENSIS LEAF JUICE, BEESWAX, DIMETHICONE, ETHYLHEXYLGLYCERIN, FRAGRANCE (PARFUM), MAGNESIUM SULFATE, MICROCRYSTALLINE WAX, MINERAL OIL, PEG-30 DIPOLYHYDROXYSTEARATE, PETROLATUM, PHENOXYETHANOL, POTASSIUM HYDROXIDE, SORBITAN SESQUIOLEATE, TOCOPHERYL ACETATE, WATER (AQUA).

QUESTIONS?

CALL 1-800-910-6874